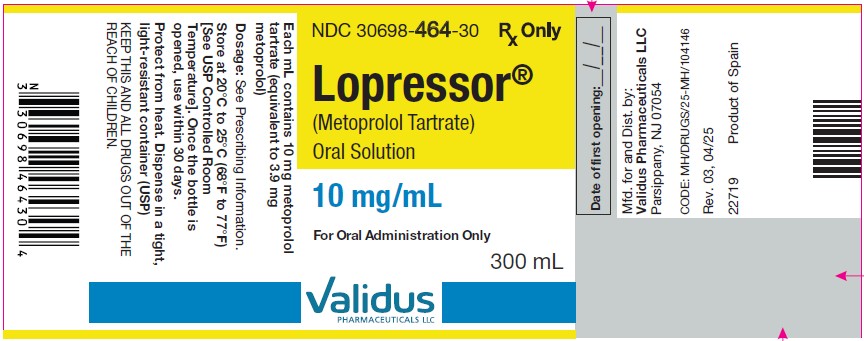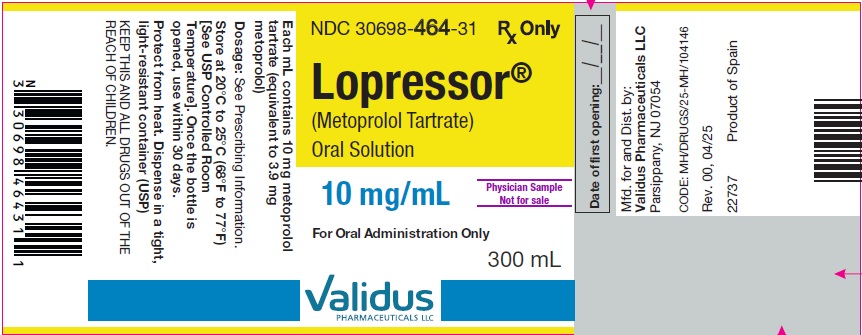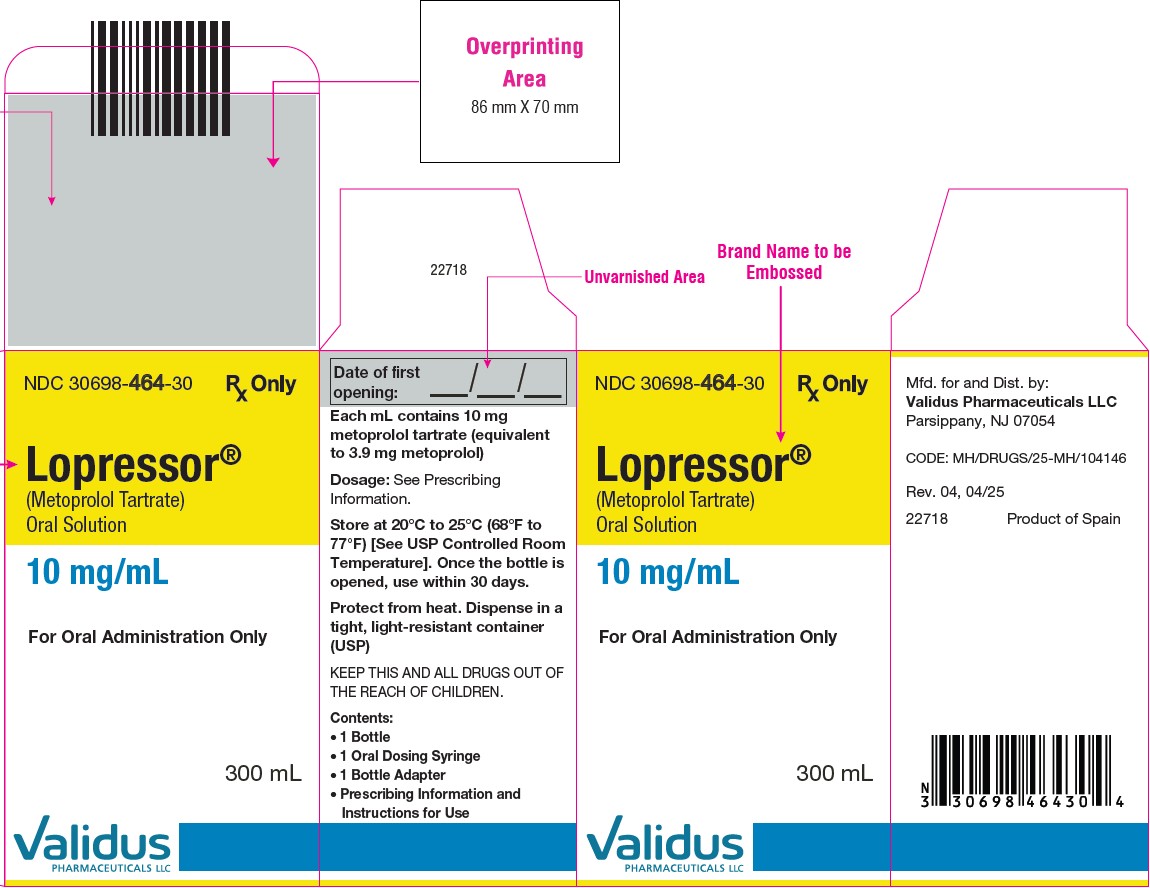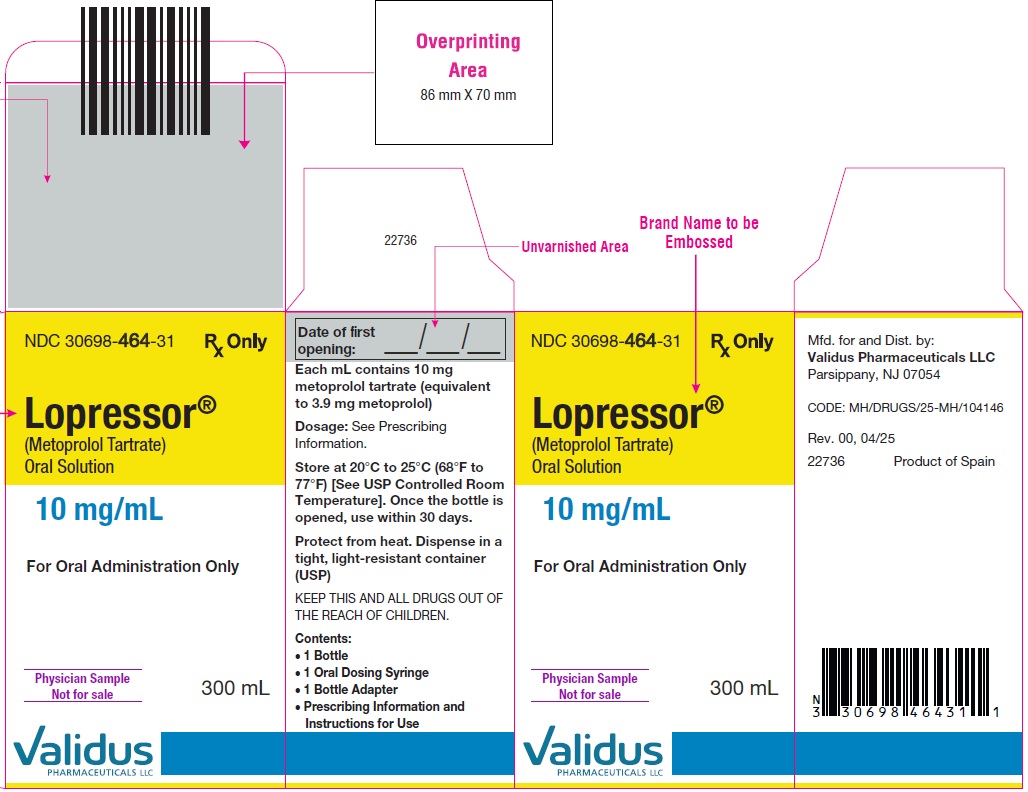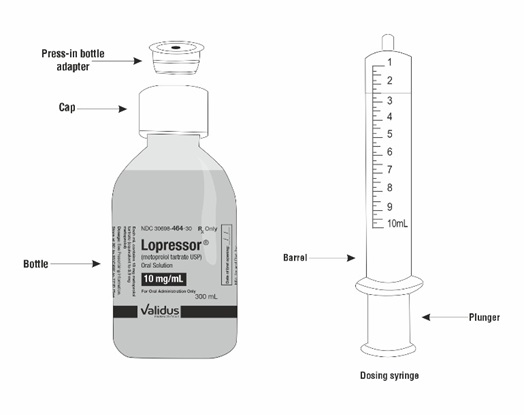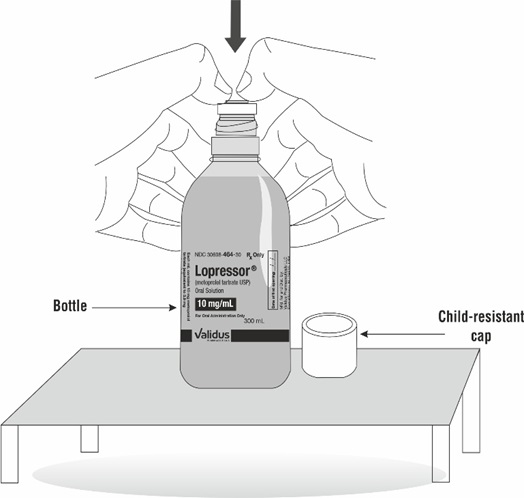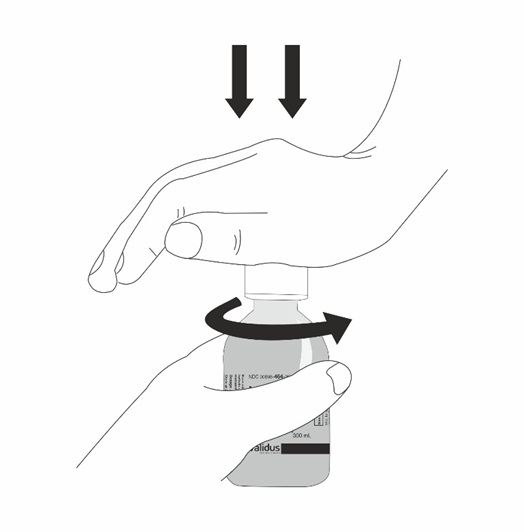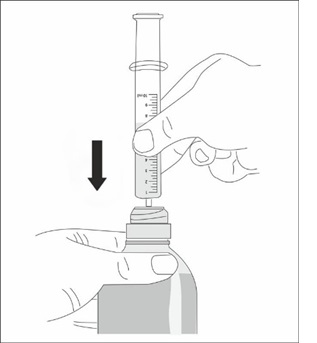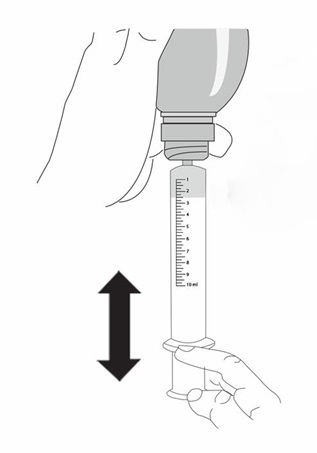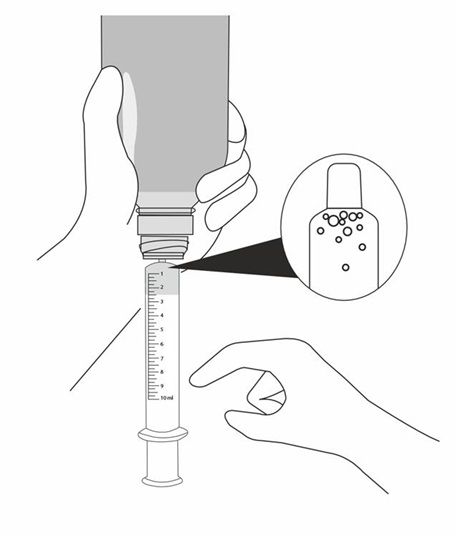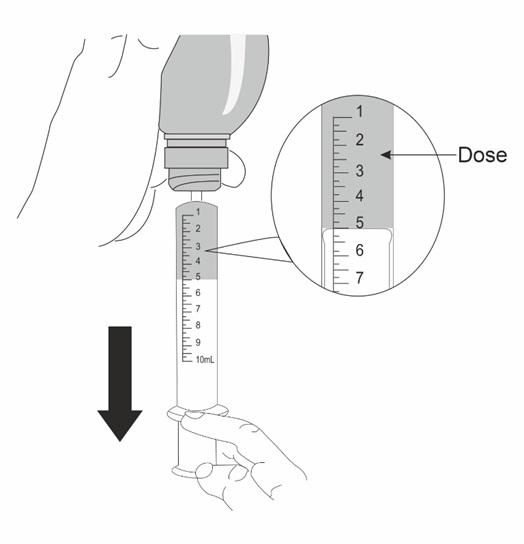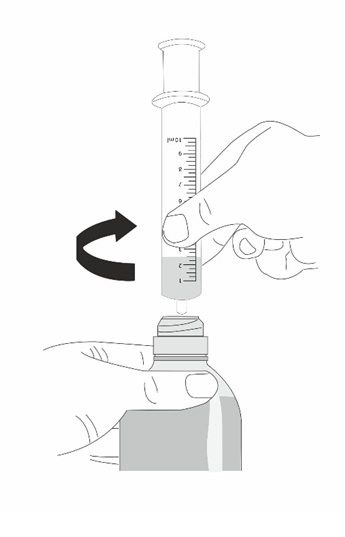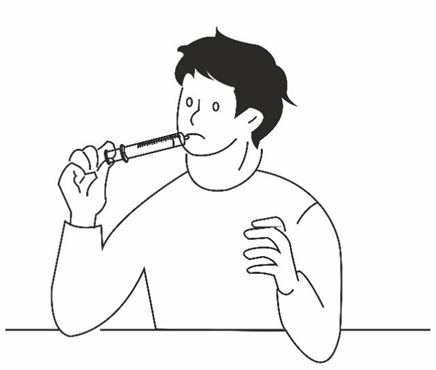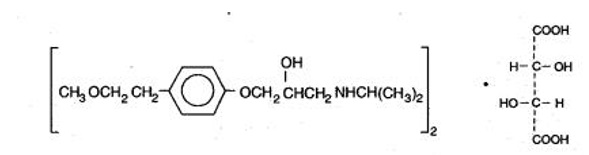 DRUG LABEL: LOPRESSOR
NDC: 30698-464 | Form: SOLUTION
Manufacturer: VALIDUS PHARMACEUTICALS LLC
Category: prescription | Type: HUMAN PRESCRIPTION DRUG LABEL
Date: 20250515

ACTIVE INGREDIENTS: METOPROLOL TARTRATE 10 mg/1 mL
INACTIVE INGREDIENTS: CITRIC ACID MONOHYDRATE; EDETATE DISODIUM; GLYCERIN; WATER; SODIUM BENZOATE; SUCRALOSE; XANTHAN GUM

HIGHLIGHTS OF PRESCRIBING INFORMATION

These highlights do not include all the information needed to use LOPRESSOR®safely and effectively. See full prescribing information for LOPRESSOR®.
LOPRESSOR®(metoprolol tartrate) oral solution
Initial U.S. Approval: 1992

1 INDICATIONS AND USAGE

LOPRESSOR is a beta-adrenergic blocker indicated in adult patients:

- For the treatment of hypertension, to lower blood pressure. Lowering blood pressure reduces the risk of fatal and non-fatal cardiovascular events, primarily strokes and myocardial infarctions. (1.1)
- In the long-term treatment of angina pectoris. (1.2)
- In the treatment of hemodynamically stable patients with definite or suspected myocardial infarction, to reduce the risk of cardiovascular mortality when used in conjunction with intravenous metoprolol therapy (1.3)

2 DOSAGE AND ADMINISTRATION

- Administer once daily with food or after a meal. Titrate at weekly or longer intervals as needed and tolerated. (2)
- Hypertension: Recommended starting dosage is 100 mg orally daily, in single or divided doses. (2.1)
- Angina Pectoris: Recommended starting dosage is 100 mg orally daily, given as two divided doses. (2.2)
- Myocardial Infarction: The starting dosage depends upon tolerance of intravenous metoprolol, see full prescribing information. (2.3)

3 DOSAGE FORMS AND STRENGTHS

- LOPRESSOR, 10 mg/mL. Each mL contains 10 mg metoprolol tartrate (equivalent to 3.9 mg metoprolol). (3)

4 CONTRAINDICATIONS

- Known hypersensitivity to product components. (4)
- Severe bradycardia: Greater than first degree heart block, or sick sinus syndrome without a pacemaker. (4)
- Cardiogenic shock or decompensated heart failure. (4)

5 WARNINGS AND PRECAUTIONS

- Abrupt cessation may exacerbate myocardial ischemia. (5.1)
- Heart Failure: Worsening cardiac failure may occur. (5.2)
- Bronchospastic Disease: Avoid beta-blockers. (5.3)
- Pheochromocytoma: Initiate therapy with an alpha blocker. (5.4)
- Major Surgery: Avoid initiation of high-dose extended-release metoprolol in patients undergoing non-cardiac surgery. Do not routinely withdraw chronic beta-blocker therapy prior to surgery. (5.5, 6.1)
- Diabetes: May mask symptoms of hypoglycemia. (5.6)
- Thyrotoxicosis: Abrupt withdrawal in patients with thyrotoxicosis might precipitate a thyroid storm. (5.7)
- Peripheral Vascular Disease: Can aggravate symptoms of arterial insufficiency. (5.9)

6 ADVERSE REACTIONS

- Most common adverse reactions: tiredness, dizziness, depression, shortness of breath, bradycardia, hypotension, diarrhea, pruritus, rash. (6.1)

To report SUSPECTED ADVERSE REACTIONS, contact Validus Pharmaceuticals LLC at 1-866-982-5438 or FDA at 1-800-FDA-1088 orwww.fda.gov/medwatch.

7 DRUG INTERACTIONS

- Catecholamine-depleting drugs may have an additive effect when given with beta-blocking agents. (7.1)
- Patients may be unresponsive to the usual doses of epinephrine used to treat allergic reaction. (7.2)
- CYP2D6 Inhibitors are likely to increase metoprolol concentration. (7.3)
- Concomitant use of glycosides, clonidine, and diltiazem and verapamil with beta-blockers can increase the risk of bradycardia. (7.4)
- Beta-blockers including metoprolol, may exacerbate the rebound hypertension that can follow the withdrawal of clonidine. (7.4)

8 USE IN SPECIFIC POPULATIONS

- Hepatic Impairment: Consider initiating LOPRESSOR therapy at low doses and gradually increase dosage to optimize therapy, while monitoring closely for adverse events. (8.6)

FULL PRESCRIBING INFORMATION

1 INDICATIONS AND USAGE

1.1 Hypertension

LOPRESSOR®is indicated for the treatment of hypertension in adult patients, to lower blood pressure. Lowering blood pressure lowers the risk of fatal and non-fatal cardiovascular events, primarily strokes and myocardial infarctions. These benefits have been seen in controlled trials of antihypertensive drugs from a wide variety of pharmacologic classes including metoprolol.

Control of high blood pressure should be part of comprehensive cardiovascular risk management, including, as appropriate, lipid control, diabetes management, antithrombotic therapy, smoking cessation, exercise, and limited sodium intake. Many patients will require more than 1 drug to achieve blood pressure goals. For specific advice on goals and management, see published guidelines, such as those of the National High Blood Pressure Education Program’s Joint National Committee on Prevention, Detection, Evaluation, and Treatment of High Blood Pressure (JNC).

Numerous antihypertensive drugs, from a variety of pharmacologic classes and with different mechanisms of action, have been shown in randomized controlled trials to reduce cardiovascular morbidity and mortality, and it can be concluded that it is blood pressure reduction, and not some other pharmacologic property of the drugs, that is largely responsible for those benefits. The largest and most consistent cardiovascular outcome benefit has been a reduction in the risk of stroke, but reductions in myocardial infarction and cardiovascular mortality also have been seen regularly.

Elevated systolic or diastolic pressure causes increased cardiovascular risk, and the absolute risk increase per mmHg is greater at higher blood pressures, so that even modest reductions of severe hypertension can provide substantial benefit. Relative risk reduction from blood pressure reduction is similar across populations with varying absolute risk, so the absolute benefit is greater in patients who are at higher risk independent of their hypertension (for example, patients with diabetes or hyperlipidemia), and such patients would be expected to benefit from more aggressive treatment to a lower blood pressure goal.

Some antihypertensive drugs have smaller blood pressure effects (as monotherapy) in black patients, and many antihypertensive drugs have additional approved indications and effects (e.g., on angina, heart failure, or diabetic kidney disease). These considerations may guide selection of therapy.

LOPRESSOR®may be administered with other antihypertensive agents.

1.2 Angina Pectoris

LOPRESSOR is indicated in the long-term treatment of angina pectoris in adult patients, to reduce angina attacks and to improve exercise tolerance.

1.3 Myocardial Infarction

LOPRESSOR is indicated in the treatment of hemodynamically stable adult patients with definite or suspected acute myocardial infarction to reduce cardiovascular mortality when used alone or in conjunction with intravenous metoprolol.

2 DOSAGE AND ADMINISTRATION

2.1 Hypertension

Individualize the dosage of LOPRESSOR Oral Solution. LOPRESSOR Oral Solution should be taken with or immediately following meals.

The usual initial dosage is 100 mg orally daily in single or divided doses. Adjust dosage at weekly (or longer) intervals until optimum blood pressure reduction is achieved. In general, the maximum effect of any given dosage level will be apparent after 1 week of therapy. The effective dosage range of LOPRESSOR Oral Solution is 100 mg to 450 mg per day. Dosages above 450 mg per day have not been studied. While once-daily dosing can maintain a reduction in blood pressure throughout the day, lower doses (especially 100 mg) may not maintain a full effect at the end of the 24-hour period. Larger or more frequent daily doses may be required. Measure blood pressure near the end of the dosing interval to determine whether satisfactory control is being maintained throughout the day.

2.2 Angina Pectoris

The dosage of LOPRESSOR Oral Solution should be individualized. LOPRESSOR Oral Solution should be taken with or immediately following meals.

The usual initial dosage is 100 mg orally daily, given in two divided doses. Gradually increase the dosage at weekly intervals until optimum clinical response has been obtained or there is a pronounced slowing of the heart rate. The effective dosage range of LOPRESSOR Oral Solution is 100 to 400 mg per day. Dosages above 400 mg per day have not been studied. If treatment is to be discontinued, reduce the dosage gradually over a period of 1 – 2 weeks [see Warnings and Precautions (5.1)].

2.3 Myocardial Infarction

See prescribing information of intravenous metoprolol for dosage instructions for intravenous therapy.

In patients who tolerate the full intravenous dose, initiate LOPRESSOR Oral Solution, 50 mg every 6 hours, 15 minutes after the last intravenous dose of metoprolol and continue for 48 hours. In the case of intolerance, reduce dose to 25 mg and administer for 48 hours. Titrate, based on tolerability, to a maintenance dosage of 100 mg twice daily. Continue therapy for at least 3 months. Although the efficacy of LOPRESSOR beyond 3 months has not been conclusively established, data from studies with other beta-blockers suggest that treatment should be continued for 1 to 3 years.

3 DOSAGE FORMS AND STRENGTHS

LOPRESSOR Oral Solution, (10 mg/mL) is a clear, colorless solution. Each mL of oral solution contains 10 mg of metoprolol tartrate equivalent to 3.90 mg of metoprolol. [see Description (11)and How Supplied/Storage and Handling (16)]

4 CONTRAINDICATIONS

LOPRESSOR is contraindicated in severe bradycardia, second- or third-degree heart block, cardiogenic shock, systolic blood pressure <100, decompensated heart failure, sick sinus syndrome (unless a permanent pacemaker is in place), and in patients who are hypersensitive to any component of this product.

5 WARNINGS AND PRECAUTIONS

5.1 Abrupt Cessation of Therapy

Following abrupt cessation of therapy with certain beta-blocking agents, exacerbations of angina pectoris and, in some cases, myocardial infarction have occurred. When discontinuing chronically administered LOPRESSOR, particularly in patients with ischemic heart disease, gradually reduce the dosage over a period of 1 to 2 weeks and monitor the patient. If angina markedly worsens or acute coronary ischemia develops, promptly reinstate LOPRESSOR, and take measures appropriate for the management of unstable angina. Warn patients not to interrupt therapy without their physician’s advice. Because coronary artery disease is common and may be unrecognized, avoid abruptly discontinuing LOPRESSOR in patients treated only for hypertension.

5.2 Heart Failure

Worsening cardiac failure may occur during up-titration of LOPRESSOR. If such symptoms occur, increase diuretics and restore clinical stability before advancing the dose of LOPRESSOR [see Dosage and Administration (2)]. It may be necessary to lower the dose of LOPRESSOR or temporarily discontinue it. Such episodes do not preclude subsequent successful titration of LOPRESSOR.

5.3 Bronchospastic Disease

Patients with bronchospastic disease, should in general, not receive beta-blockers, including LOPRESSOR.Because of its relative beta1cardio-selectivity, however, LOPRESSOR may be used in patients with bronchospastic disease who do not respond to, or cannot tolerate, other antihypertensive treatment. Because beta1-selectivity is not absolute, use the lowest possible dose of LOPRESSOR. Bronchodilators, including beta2-agonists, should be readily available or administered concomitantly [see Dosage and Administration (2)].

5.4 Pheochromocytoma

If LOPRESSOR is used in the setting of pheochromocytoma, it should be given in combination with an alpha blocker, and only after the alpha blocker has been initiated. Administration of beta- blockers alone in the setting of pheochromocytoma has been associated with a paradoxical increase in blood pressure due to the attenuation of beta-mediated vasodilatation in skeletal muscle.

5.5 Major Surgery

Avoid initiation of a high-dose regimen of beta-blocker therapy in patients undergoing non-cardiac surgery, since such use in patients with cardiovascular risk factors has been associated with bradycardia, hypotension, stroke and death.

Chronically administered beta-blocking therapy should not be routinely withdrawn prior to major surgery, however, the impaired ability of the heart to respond to reflex adrenergic stimuli may augment the risks of general anesthesia and surgical procedures.

5.6 Hypoglycemia

Beta-blockers may prevent early warning signs of hypoglycemia, such as tachycardia, and increase the risk for severe or prolonged hypoglycemia at any time during treatment, especially in patients with diabetes mellitus or children and patients who are fasting (i.e., surgery, not eating regularly, or are vomiting). If severe hypoglycemia occurs, patients should be instructed to seek emergency treatment.

5.7 Thyrotoxicosis

Beta-adrenergic blockade may mask certain clinical signs of hyperthyroidism, such as tachycardia. Abrupt withdrawal of beta-blockade may precipitate a thyroid storm.

5.8 Risk of Anaphylactic Reaction

While taking beta-blockers, patients with a history of severe anaphylactic reaction to a variety of allergens may be more reactive to repeated challenge, either accidental, diagnostic, or therapeutic. Such patients may be unresponsive to the usual doses of epinephrine used to treat allergic reaction.

5.9 Peripheral Vascular Disease

Beta-blockers can precipitate or aggravate symptoms of arterial insufficiency in patients with peripheral vascular disease.

6 ADVERSE REACTIONS

The following adverse reactions are described elsewhere in labeling:

- Worsening angina or myocardial infarction [see Warnings and Precautions (5)]
- Worsening heart failure [see Warnings and Precautions (5)].
- Worsening AV block [see Contraindications (4)].

6.1 Clinical Trials Experience

Because clinical trials are conducted under widely varying conditions, adverse reaction rates observed in the clinical trials of a drug cannot be directly compared to rates in the clinical trials of another drug and may not reflect the rates observed in practice.

Hypertension and Angina

Most adverse effects have been mild and transient.

Central Nervous System:Tiredness and dizziness have occurred in about 10% of patients. Depression has been reported in about 5 of 100 patients. Mental confusion and short-term memory loss have been reported. Headache, nightmares, and insomnia have also been reported.

Cardiovascular:Shortness of breath and bradycardia have occurred in approximately 3% of patients. Cold extremities; arterial insufficiency, usually of the Raynaud type; palpitations; heart failure exacerbations; peripheral edema; and hypotension have been reported in about 1% of patients. Gangrene in patients with pre-existing severe peripheral circulatory disorders has also been reported. [see Contraindications (4)and Warnings and Precautions (5.2)].

Respiratory:Wheezing (bronchospasm) and dyspnea have been reported in about 1% of patients

[see Warnings and Precautions (5.3)]. Rhinitis has also been reported.

Gastrointestinal:Diarrhea has occurred in about 5% of patients. Nausea, dry mouth, gastric pain, constipation, flatulence, and heartburn have been reported in about 1% of patients. Vomiting was a common occurrence.

Hypersensitive Reactions:Pruritus or rash have occurred in about 5% of patients. Photosensitivity and worsening of psoriasis has been reported.

Miscellaneous:Peyronie’s disease, musculoskeletal pain, blurred vision, and tinnitus has been reported.

Myocardial Infarction

In general, the adverse reactions observed in trials with metoprolol in MI are consistent with the hypertension and angina experience.

In a randomized comparison of LOPRESSOR and placebo in the setting of acute MI the following adverse reactions were reported:

 | LOPRESSOR | Placebo
Hypotension (systolic BP < 90 mm Hg) | 27.4% | 23.2%
Bradycardia (heart rate < 40 beats/min) | 15.9% | 6.7%
Second- or third-degree heart block | 4.7% | 4.7%
First-degree heart block (P-R ≥ 0.26 sec) | 5.3% | 1.9%
Heart failure | 27.5% | 29.6%

6.2 Post-Marketing Experience

The following adverse reactions have been identified during post approval use of LOPRESSOR. Because these reactions are reported voluntarily from a population of uncertain size, it is not always possible to reliably estimate their frequency or establish a causal relationship to drug exposure.

Central Nervous System:Reversible mental depression progressing to catatonia; an acute reversible syndrome characterized by disorientation for time and place, short-term memory loss, emotional lability, slightly clouded sensorium, and decreased performance on neuropsychometrics.

Cardiovascular:Intensification of AV block [see Contraindications (4)].

Hematologic:Agranulocytosis, nonthrombocytopenic purpura and thrombocytopenic purpura.

Hypersensitive Reactions:Fever combined with aching and sore throat, laryngospasm and respiratory distress.

Laboratory Findings:

Increase in blood triglycerides, elevated transaminase and decrease in High Density Lipoprotein (HDL)

7 DRUG INTERACTIONS

7.1 Catecholamine Depleting Drugs

Catecholamine depleting drugs (e.g., reserpine, monoamine oxidase (MAO) inhibitors) may have an additive effect when given with beta-blocking agents. Observe patients treated with LOPRESSOR plus a catecholamine depletor for evidence of hypotension or marked bradycardia, which may produce vertigo, syncope, or postural hypotension.

7.2 Epinephrine

While taking beta-blockers, patients with a history of severe anaphylactic reactions to a variety of allergens may be more reactive to repeated challenge and may be unresponsive to the usual doses of epinephrine used to treat an allergic reaction.

7.3 CYP2D6 Inhibitors

Drugs that are strong inhibitors of CYP2D6 such as quinidine, fluoxetine, paroxetine, and propafenone were shown to double metoprolol concentrations. While there is no information about moderate or weak inhibitors, these too are likely to increase metoprolol concentration. Increases in plasma concentration decrease the cardioselectivity of metoprolol [see Clinical Pharmacology (12.3)]. Monitor patients closely, when the combination cannot be avoided.

7.4 Negative Chronotropes

Digitalis glycosides, clonidine, diltiazem and verapamil slow atrioventricular conduction and decrease heart rate. Concomitant use with beta-blockers can increase the risk of bradycardia.

If clonidine and a beta-blocker, such as metoprolol are coadministered, withdraw the beta-blocker several days before the gradual withdrawal of clonidine because beta-blockers may exacerbate the rebound hypertension that can follow the withdrawal of clonidine. If replacing clonidine by beta- blocker therapy, delay the introduction of beta-blockers for several days after clonidine administration has stopped .

8 USE IN SPECIFIC POPULATIONS

8.1 Pregnancy

Risk Summary

Available data from published observational studies have not demonstrated an association of adverse developmental outcomes with maternal use of metoprolol during pregnancy (see Data).Untreated hypertension and myocardial infarction during pregnancy can lead to adverse outcomes for the mother and the fetus (see Clinical Considerations).In animal reproduction studies, metoprolol has been shown to increase post-implantation loss and decrease neonatal survival in rats at oral dosages of 500 mg/kg/day, approximately 11 times the daily dose of 450 mg in a 60- kg patient on a mg/m^2basis.

All pregnancies have a background risk of birth defect, loss, or other adverse outcomes. The estimated background risk of major birth defects and miscarriage for the indicated population is unknown. In the U.S. general population, the estimated background risk of major birth defects and miscarriage in clinically recognized pregnancies is 2 to 4% and 15 to 20%, respectively.

Clinical consideration

Disease-associated maternal and/or embryo/fetal risk

Hypertension in pregnancy increases the maternal risk for pre-eclampsia, gestational diabetes, premature delivery, and delivery complications (e.g., need for cesarean section, and post-partum hemorrhage). Hypertension increases the fetal risk for intrauterine growth restriction and intrauterine death. Pregnant women with hypertension should be carefully monitored and managed accordingly.

Fetal/Neonatal adverse reactions

Metoprolol crosses the placenta. Neonates born to mothers who are receiving metoprolol during pregnancy, may be at risk for hypotension, hypoglycemia, bradycardia, and respiratory depression. Observe neonates and manage accordingly.

Data

Human Data

Data from published observational studies did not demonstrate an association of major congenital malformations and use of metoprolol in pregnancy. The published literature has reported inconsistent findings of intrauterine growth retardation, preterm birth and perinatal mortality with maternal use of metoprolol during pregnancy; however, these studies have methodological limitations hindering interpretation. Methodological limitations include retrospective design, concomitant use of other medications, and other unadjusted confounders that may account for the study findings including the underlying disease in the mother. These observational studies cannot definitely establish or exclude any drug-associated risk during pregnancy.

Animal Data

Metoprolol has been shown to increase post-implantation loss and decrease neonatal survival in rats at oral dosages of 500 mg/kg/day, i.e., 11 times, on a mg/m^2basis, the daily dose of 450 mg in a 60-kg patient.

No fetal abnormalities were observed when pregnant rats received metoprolol orally up to a dose of 200 mg/kg/day, i.e., 4 times, the daily dose of 400mg in a 60-kg patient.

8.2 Lactation

Risk Summary

Limited available data from published literature report that metoprolol is present in human milk. The estimated daily infant dose of metoprolol received from breastmilk ranges from 0.05 mg to less than 1 mg. The estimated relative infant dosage was 0.5% to 2% of the mother's weight- adjusted dosage (see Data).No adverse reactions of metoprolol on the breastfed infant have been identified. There is no information regarding the effects of metoprolol on milk production.

Clinical consideration

Monitoring for adverse reactions

For a lactating woman who is a slow metabolizer of metoprolol, monitor the breastfed infant for bradycardia and other symptoms of beta-blockade such as dry mouth, skin or eyes, diarrhea or constipation. In a report of 6 mothers taking metoprolol, none reported adverse effects in her breastfed infant.

Data

Limited published cases estimate the infant daily dose of metoprolol received from breast milk range from 0.05 mg to less than 1 mg.

In 2 women who were taking unspecified amount of metoprolol, milk samples were taken after one dose of metoprolol. The estimated amount of metoprolol and alpha-hydroxymetoprolol in breast milk is reported to be less than 2% of the mother's weight-adjusted dosage.

In a small study, breast milk was collected every 2 to 3 hours over one dosage interval, in three mothers (at least 3 months postpartum) who took metoprolol of unspecified amount. The average amount of metoprolol present in breast milk was 71.5 mcg/day (range 17.0 to 158.7). The average relative infant dosage was 0.5% of the mother's weight-adjusted dosage.

8.3 Females and Males of Reproductive Potential

Risk Summary

Based on the published literature, beta-blockers (including metoprolol) may cause erectile dysfunction and inhibit sperm motility. In animal fertility studies, metoprolol has been associated with reversible adverse effects on spermatogenesis starting at oral dose level of 3.5 mg/kg in rats, which would correspond to a dose of 34 mg/day in humans in mg/m^2equivalent, although other studies have shown no effect of metoprolol on reproductive performance in male rats.

No evidence of impaired fertility due to metoprolol was observed in rats [see Nonclinical Toxicology (13.1)].

8.4 Pediatric Use

Safety and effectiveness of LOPRESSOR have not been established in pediatric patients.

8.5 Geriatric Use

Clinical studies of LOPRESSOR in hypertension did not include sufficient numbers of subjects aged 65 and over to determine whether they respond differently from younger subjects. Other reported clinical experience in hypertensive patients has not identified differences in responses between elderly and younger patients.

In worldwide clinical trials of LOPRESSOR in myocardial infarction, where approximately 478 patients were over 65 years of age (0 over 75 years of age), no age-related differences in safety and effectiveness were found. Other reported clinical experience in myocardial infarction has not identified differences in response between the elderly and younger patients.

In general, use a low initial starting dose in elderly patients given their greater frequency of decreased hepatic, renal, or cardiac function, and of concomitant disease or other drug therapy.

8.6 Hepatic Impairment

No studies have been performed with LOPRESSOR in patients with hepatic impairment. Because LOPRESSOR is metabolized by the liver, metoprolol blood levels are likely to increase substantially with poor hepatic function. Therefore, initiate therapy at doses lower than those recommended for a given indication; and increase doses gradually in patients with impaired hepatic function.

8.7 Renal Impairment

The systemic availability and half-life of metoprolol in patients with renal failure do not differ to a clinically significant degree from those in normal subjects. No reduction in dosage is needed in patients with chronic renal failure [see Clinical Pharmacology (12.3)].

10 OVERDOSAGE

Signs and Symptoms - Overdosage of LOPRESSOR may lead to severe bradycardia, hypotension, and cardiogenic shock. Clinical presentation can also include: atrioventricular block, heart failure, bronchospasm, hypoxia, impairment of consciousness/coma, nausea and vomiting.

Treatment – Consider treating the patient with intensive care. Patients with myocardial infarction or heart failure may be prone to significant hemodynamic instability. Beta-blocker overdose may result in significant resistance to resuscitation with adrenergic agents, including beta-agonists. On the basis of the pharmacologic actions of metoprolol, employ the following measures.

Hemodialysis is unlikely to make a useful contribution to metoprolol elimination [see Clinical Pharmacology (12.3)].

Bradycardia: Evaluate the need for atropine, adrenergic-stimulating drugs or pacemaker to treat bradycardia and conduction disorders.

Hypotension: Treat underlying bradycardia. Consider intravenous vasopressor infusion, such as dopamine or norepinephrine.

Heart failure and shock: May be treated when appropriate with suitable volume expansion, injection of glucagon (if necessary, followed by an intravenous infusion of glucagon), intravenous administration of adrenergic drugs such as dobutamine, with α1 receptor agonistic drugs added in presence of vasodilation.

Bronchospasm: Can usually be reversed by bronchodilators.

11 DESCRIPTION

LOPRESSOR Oral Solution contain metoprolol tartrate, a selective beta1-adrenoreceptor blocking agent. Metoprolol tartrate is (±)-1-(Isopropylamino)-3-[p-(2-methoxyethyl) phenoxy]-2-propanol L-(+)- tartrate (2:1) salt, and its structural formula is

Metoprolol tartrate, USP is a white, practically odorless, crystalline powder with a molecular weight of 684.82 g/mol. It is very soluble in water; freely soluble in methylene chloride, in chloroform, and in alcohol; slightly soluble in acetone; and insoluble in ether.

LOPRESSOR: Each mL contains 10 mg metoprolol tartrate (equivalent to 3.9 mg metoprolol) and the following inactive ingredients: citric acid monohydrate, disodium edetate, glycerin, purified water, sodium benzoate, sucralose, and xanthan gum.

12 CLINICAL PHARMACOLOGY

12.1 Mechanism of Action

Metoprolol is a beta1-selective (cardioselective) adrenergic receptor blocking agent. This preferential effect is not absolute, however, and at higher plasma concentrations, metoprolol also inhibits beta2-adrenoreceptors, chiefly located in the bronchial and vascular musculature.

Metoprolol has no intrinsic sympathomimetic activity, and membrane-stabilizing activity is detectable only at plasma concentrations much greater than required for beta-blockade. Animal and human experiments indicate that metoprolol slows the sinus rate and decreases AV nodal conduction.

The relative beta1-selectivity of metoprolol has been confirmed by the following: (1) In normal subjects, metoprolol is unable to reverse the beta2-mediated vasodilating effects of epinephrine. This contrasts with the effect of nonselective beta-blockers, which completely reverse the vasodilating effects of epinephrine. (2) In asthmatic patients, metoprolol reduces FEV1and FVC significantly less than a nonselective beta-blocker, propranolol, at equivalent beta1-receptor blocking doses.

Hypertension:The mechanism of the antihypertensive effects of beta-blocking agents has not been elucidated. However, several possible mechanisms have been proposed: (1) competitive antagonism of catecholamines at peripheral (especially cardiac) adrenergic neuron sites, leading to decreased cardiac output; (2) a central effect leading to reduced sympathetic outflow to the periphery; and (3) suppression of renin activity.

Angina Pectoris:By blocking catecholamine-induced increases in heart rate, in velocity and extent of myocardial contraction, and in blood pressure, metoprolol reduces the oxygen requirements of the heart at any given level of effort, thus making it useful in the long-term management of angina pectoris.

Heart Failure:The precise mechanism for the beneficial effects of beta-blockers in heart failure has not been elucidated.

12.2 Pharmacodynamics

Clinical pharmacology studies have confirmed the beta-blocking activity of metoprolol in man, as shown by (1) reduction in heart rate and cardiac output at rest and upon exercise, (2) reduction of systolic blood pressure upon exercise, (3) inhibition of isoproterenol-induced tachycardia, and (4) reduction of reflex orthostatic tachycardia.

The relationship between plasma metoprolol levels and reduction in exercise heart rate is independent of the pharmaceutical formulation. Beta1-blocking effects in the range of 30-80% of the maximal effect (approximately 8 to 23% reduction in exercise heart rate) correspond to metoprolol plasma concentrations from 30 to 540 nmol/L. The relative beta1-selectivity of metoprolol diminishes and blockade of beta2-adrenoceptors increases at plasma concentration above 300 nmol/L.

Significant beta-blocking effect (as measured by reduction of exercise heart rate) occurs within 1 hour after oral administration, and its duration is dose-related. For example, a 50% reduction of the maximum effect after single oral doses of 20, 50, and 100 mg occurred at 3.3, 5.0, and 6.4 hours, respectively, in normal subjects. After repeated oral dosages of 100 mg twice daily, a significant reduction in exercise systolic blood pressure was evident at 12 hours. When the drug was infused over a 10-minute period, in normal volunteers, maximum beta-blockade was achieved at approximately 20 minutes. Equivalent maximal beta-blocking effect is achieved with oral and intravenous doses in the ratio of approximately 2.5:1.

There is a linear relationship between the log of plasma levels and reduction of exercise heart rate. However, antihypertensive activity does not appear to be related to plasma levels. Because of variable plasma levels attained with a given dose and lack of a consistent relationship of antihypertensive activity to dose, selection of proper dosage requires individual titration.

In several studies of patients with acute myocardial infarction, intravenous followed by oral administration of LOPRESSOR caused a reduction in heart rate, systolic blood pressure and cardiac output. Stroke volume, diastolic blood pressure and pulmonary artery end diastolic pressure remained unchanged.

12.3 Pharmacokinetics

Absorption:The estimated oral bioavailability of immediate release metoprolol is about 50% because of pre-systemic metabolism which is saturable leading to non-proportionate increase in the exposure with increased dose.

Distribution:Metoprolol is extensively distributed with a reported volume of distribution of 3.2 to 5.6 L/kg. About 10% of metoprolol in plasma is bound to serum albumin. Metoprolol is known to cross the placenta and is found in breast milk. Metoprolol is also known to cross the blood brain barrier following oral administration and CSF concentrations close to that observed in plasma have been reported. Metoprolol is not a significant P-glycoprotein substrate.

Elimination:Elimination of LOPRESSOR is mainly by biotransformation in the liver. The mean elimination half-life of metoprolol is 3 to 4 hours; in poor CYP2D6 metabolizers the half-life may be 7 to 9 hours.

Metabolism:LOPRESSOR is primarily metabolized by CYP2D6. Metoprolol is a racemic mixture of R- and S- enantiomers, and when administered orally, it exhibits stereoselective metabolism that is dependent on oxidation phenotype.

Excretion

Approximately 95% of the dose can be recovered in urine. In most subjects (extensive metabolizers), less than 5% of an oral dose and less than 10% of an intravenous dose are excreted as unchanged drug in the urine. In poor metabolizers, up to 30% or 40% of oral or intravenous doses, respectively, may be excreted unchanged; the rest is excreted by the kidneys as metabolites that appear to have no beta-blocking activity. The renal clearance of the stereo-isomers of metoprolol does not exhibit stereo-selectivity in renal excretion.

Specific populations

Geriatric patients:The geriatric population may show slightly higher plasma concentrations of metoprolol as a combined result of a decreased metabolism of the drug in elderly population and a decreased hepatic blood flow. However, this increase is not clinically significant or therapeutically relevant.

Renal Impairment:The systemic availability and half-life of LOPRESSOR in patients with renal failure do not differ to a clinically significant degree from those in normal subjects.

Hepatic Impairment:Since the drug is primarily eliminated by hepatic metabolism, hepatic impairment may impact the pharmacokinetics of metoprolol.

Drug Interaction Studies

Metoprolol is metabolized predominantly by CYP2D6. In healthy subjects with CYP2D6 extensive metabolizer phenotype, coadministration of quinidine 100 mg, a potent CYP2D6 inhibitor, and immediate-release metoprolol 200 mg tripled the concentration of S-metoprolol and doubled the metoprolol elimination half-life. In four patients with cardiovascular disease, coadministration of propafenone 150 mg t.i.d. with immediate-release metoprolol 50 mg t.i.d. increased the steady-state metoprolol concentration 2- to 5-fold compared to metoprolol alone. Extensive metabolizers who concomitantly use CYP2D6 inhibiting drugs will have increased (several-fold) metoprolol blood levels, decreasing metoprolol's cardioselectivity [see Drug Interactions (7.2)] .

12.5 Pharmacogenomics

CYPD6 is absent (poor metabolizers) in about 8% of Caucasians and about 2% of most other populations. Poor CYP2D6 metabolizers exhibit several- fold higher plasma concentrations of Metoprolol Tartrate than extensive metabolizers with normal CYP2D6 activity thereby decreasing Metoprolol Tartrate cardioselectivity.

13 NONCLINICAL TOXICOLOGY

13.1 Carcinogenesis, Mutagenesis, Impairment of Fertility

Long-term studies in animals have been conducted to evaluate the carcinogenic potential of metoprolol tartrate. In 2-year studies in rats at three oral dosage levels of up to 800 mg/kg/day (19 times, on a mg/m^2basis, the daily dose of 400 mg for a 60-kg patient), there was no increase in the development of spontaneously occurring benign or malignant neoplasms of any type. The only histologic changes that appeared to be drug related were an increased incidence of generally mild focal accumulation of foamy macrophages in pulmonary alveoli and a slight increase in biliary hyperplasia. In a 21-month study in Swiss albino mice at three oral dosage levels of up to 750 mg/kg/day (9 times, on a mg/m^2basis, the daily dose of 400 mg for a 60-kg patient), benign lung tumors (small adenomas) occurred more frequently in female mice receiving the highest dose than in untreated control animals. There was no increase in malignant or total (benign plus malignant) lung tumors, nor in the overall incidence of tumors or malignant tumors. This 21-month study was repeated in CD-1 mice, and no statistically or biologically significant differences were observed between treated and control mice of either sex for any type of tumor.

All genotoxicity tests performed on metoprolol tartrate (a dominant lethal study in mice, chromosome studies in somatic cells, a Salmonella/mammalian-microsome mutagenicity test, and a nucleus anomaly test in somatic interphase nuclei) and metoprolol succinate (a Salmonella/mammalian-microsome mutagenicity test) were negative.

No evidence of impaired fertility due to metoprolol tartrate was observed in a study performed in rats at doses up to 55.5 times, on a mg/m^2basis, the daily dose of 450 mg in a 60-kg patient.

14 CLINICAL STUDIES

14.1 Hypertension

In controlled clinical studies, LOPRESSOR has been shown to be an effective antihypertensive agent when used alone or as concomitant therapy with thiazide-type diuretics, at dosages of 100 mg to 450 mg daily. In controlled, comparative, clinical studies, LOPRESSOR has been shown to be as effective an antihypertensive agent as propranolol, methyldopa, and thiazide-type diuretics, to be equally effective in supine and standing positions.

14.2 Angina Pectoris

In controlled clinical trials, LOPRESSOR, administered two or four times daily, has been shown to be an effective antianginal agent, reducing the number of angina attacks and increasing exercise tolerance. The dosage used in these studies ranged from 100 mg to 400 mg daily. A controlled, comparative, clinical trial showed that LOPRESSOR was indistinguishable from propranolol in the treatment of angina pectoris.

14.3 Myocardial Infarction

In a large (1395 patients randomized), double-blind, placebo-controlled clinical study, LOPRESSOR was shown to reduce 3-month mortality by 36% in patients with suspected or definite myocardial infarction.

Patients were randomized and treated as soon as possible after their arrival in the hospital, once their clinical condition had stabilized and their hemodynamic status had been carefully evaluated. Subjects were ineligible if they had hypotension, bradycardia, peripheral signs of shock, and/or more than minimal basal rales as signs of congestive heart failure. Initial treatment consisted of intravenous followed by oral administration of LOPRESSOR or placebo, given in a coronary care or comparable unit. Oral maintenance therapy with LOPRESSOR or placebo was then continued for 3 months. After this double-blind period, all patients were given LOPRESSOR and followed up to 1 year.

The median delay from the onset of symptoms to the initiation of therapy was 8 hours in both the LOPRESSOR - and placebo-treatment groups. Among patients treated with LOPRESSOR, there were comparable reductions in 3-month mortality for those treated early (≤ 8 hours) and those in whom treatment was started later. Significant reductions in the incidence of ventricular fibrillation and in chest pain following initial intravenous therapy were also observed with LOPRESSOR and were independent of the interval between onset of symptoms and initiation of therapy.

In this study, patients treated with metoprolol received the drug both very early (intra-venously) and during a subsequent 3-month period, while placebo patients received no beta-blocker treatment for this period. The study thus was able to show a benefit from the overall metoprolol regimen but cannot separate the benefit of very early intravenous treatment from the benefit of later beta- blocker therapy. Nonetheless, because the overall regimen showed a clear beneficial effect on survival without evidence of an early adverse effect on survival, one acceptable dosage regimen is the precise regimen used in the trial. Because the specific benefit of very early treatment remains to be defined however, it is also reasonable to administer the drug orally to patients at a later time as is recommended for certain other beta-blockers.

16 HOW SUPPLIED/STORAGE AND HANDLING

LOPRESSOR®contains 10 mg/mL of Metoprolol Tartrate. Each mL contains 10 mg metoprolol tartrate (equivalent to 3.9 mg metoprolol). It is a clear, colorless solution and is supplied in the bottle of:

- 300 mL white, opaque, HDPE bottle NDC 30698-464-30 (10 mg/mL) with child-resistant cap along with a 10 mL calibrated oral dosing syringe and press-in bottle adapter.
- 300 mL white, opaque, HDPE bottle (Physician Sample) NDC 30698-464-31 (10 mg/mL) with child-resistant cap along with a 10 mL calibrated oral dosing syringe and press-in bottle adapter.

The bottle, dosing syringe, and press-in bottle adapter are placed in a carton.

Storage:

Store at 20°C to 25°C (68°F to 77°F); excursions permitted between 15°C to 30°C (59°F to 86°F). [See USP Controlled Room Temperature.] Once the bottle is opened, use within 30 days. Protect from heat.

Dispense in a tight, light-resistant container (USP).

17 PATIENT COUNSELING INFORMATION

Advise the patient to read the FDA-approved patient labeling (Instructions for Use).

Advise patients to take LOPRESSOR regularly and continuously, as directed, preferably with or immediately following meals. If a dose is missed, the patient should take only the next scheduled dose (without doubling it). Patients should not interrupt or discontinue LOPRESSOR without consulting the physician.

Advise patients (1) to avoid operating automobiles and machinery or engaging in other tasks requiring alertness until the patient’s response to therapy with LOPRESSOR has been determined; (2) to contact the physician if any difficulty in breathing occurs; (3) to inform the physician or dentist before any type of surgery that he or she is taking LOPRESSOR.

Inform patients or caregivers that there is a risk of hypoglycemia when Metoprolol Tartrate is given to patients who are fasting or who are vomiting. Monitor for symptoms of hypoglycemia.

Manufactured for and Distributed by:
Validus Pharmaceuticals LLC
Parsippany, NJ 07054
info@validuspharma.com
www.validuspharma.com
1-866-982-5438

©2025 Validus Pharmaceuticals LLC

Revised. 00, 04/2025

INSTRUCTIONS FOR USE

LOPRESSOR®(Lo-pres-sor)

(Metoprolol Tartrate Oral Solution)

This Instructions for Use contains information on how to take LOPRESSOR.

Important Information You Need to Know Before Taking LOPRESSOR:

- Read these instructions carefully to learn how to prepare and take LOPRESSOR correctly.
- LOPRESSOR is for oral use only (taken by mouth).
- Take LOPRESSOR with a meal or right after a meal.
- Use only the oral dosing syringe and bottle adapter that come with LOPRESSOR to measure and take your medicine.
- Check the expiration date on the LOPRESSOR bottle and carton. Do not take LOPRESSOR after the expiration date has passed.

Storing LOPRESSOR

- Store LOPRESSOR at room temperaturebetween 68°F to 77°F (20°C to 25°C).
- Keep LOPRESSOR away from heat.

Supplies included in the LOPRESSOR Carton

- A press-in bottle adapterthat you push into the neck of the bottle. After it is inserted, the bottle adapter must always stay in the bottle.
- A bottlecontaining medicine, with a child-resistant cap. Always put the child-resistant cap back on the bottle and close it tightly after use.
- A 10 milliliter (mL) oral dosing syringethat fits into the bottle adapter to withdraw and measure the prescribed dose of medicine from the bottle.

Step 1: Preparing the Bottle

- Remove the child-resistant cap by pushing it firmlydown and turning it counterclockwise – to the left (as shown on the top of the cap).
  Note:Save the cap so you can close the bottle after each use.
- Hold the open bottle upright on a table and push the bottle adapter firmlyinto the neck of the bottle as far as you can.
- Put the cap back on the bottle and close it tightly by turning clockwise to make sure that the bottle adapter has been fully forced into the neck of the bottle.
  Note: You may not be able to push the bottle adapter fully down, but it will be forced into the bottle when you screw the cap back on.
  Now the bottle is ready to use with the syringe. The bottle adapter must always stay in the bottle. Do notremove the bottle adapter. The child-resistant cap should seal the bottle in between use.

Step 2: Measuring the Dose of LOPRESSOR

- Push and turn the child-resistant cap counterclockwise to open the bottle.
  Note:Always put the cap tightly back on the bottle after use.

- Check that the plunger is pushed all the way down inside the barrel of the syringe.
- Keep the bottle upright and push the tip of the syringe firmlyinto the hole in the bottle adapter.

Step 3:

- Hold the syringe in place and carefully turn the bottle upside down.
- Check the oral dosing syringe to find the right dose in milliliters (mL) that has been prescribed by your healthcare provider.
- Slowly pull the plunger out to fill the oral dosing syringe slightly past your prescribed dose line to help remove any air bubbles.

Step 4:

- Tap the syringe barrel to move air bubbles to the top. Doing this helps set the correct dose.
- Push the plunger down slowly just far enough to completely push out any large or small air bubbles that may be trapped in the syringe.

Step 5:

- Slowly pull the plunger out until the top edge of the plunger is exactly level with the marker on the syringe barrel for the prescribed dose. See Figure for an example of a dose of 5 mL.
  Note:If the prescribed dose is more than 10 mL, you will need to repeat steps 2 through 7 to refill the syringe and to take your full dose.
  Ask your pharmacist or healthcare provider to show you how to measure your dose if you are not sure.

Step 6:

- Carefully turn the bottle upright.
- Place the bottle on the table.
- Take out the syringe by gently twisting it out of the plastic adapter. The plastic adapter should stay in the bottle.
- Check that the correct dose in mL is in the oral dosing syringe.
- If the correct dose is not in the oral dosing syringe:
  - Put the tip of the syringe back into the bottle adapter and push the plunger to the bottom of the barrel to empty the contents of the syringe.
  - Repeat steps 2 through 6.

Step 7: Taking the dose of LOPRESSOR

- Important: Sit in an upright position when taking LOPRESSOR.
- Place the oral dosing syringe gently into your mouth and close the mouth tightly around the barrel of the syringe.
- Push the plunger down slowlyto make sure that you swallow all the medicine.
- Check to make sure that there is no medicine left in the oral dosing syringe.
- If the prescribed dose is more than 10 mL, repeat steps 2 through 7.

Step 8: Cleaning up

- Put the child-resistant cap tightly back on the bottle to close the bottle after use.
- After you take your dose of medicine, rinse the syringe with warm water and allow it to dry thoroughly before you use it again.

Step 9: Disposing of LOPRESSOR

- Safely throw away medicine that is expired or no longer needed.
- Do not throw away any medicines in your sink (wastewater) or the household trash. Ask your pharmacist how to throw away medicines you no longer use. These measures will help to protect the environment.
- Keep LOPRESSOR and all medicines out of the reach of children.

Manufactured for and distributed by:

Validus Pharmaceuticals LLC

Parsippany, NJ 07054

info@validuspharma.com
www.validuspharma.com
1-866-982-5438
© 2025 Validus Pharmaceuticals LLC

This Instructions for Use has been approved by the U.S. Food and Drug Administration. Issued 04/2025

PRINCIPAL DISPLAY PANEL

LOPRESSOR®(Metoprolol Tartrate) Oral Solution 10 mg/mL - NDC 30698-464-30 - 300 mL Bottle Label

LOPRESSOR®(Metoprolol Tartrate) Oral Solution 10 mg/mL - NDC 30698-464-30 - 300 mL Carton Label

LOPRESSOR® (Metoprolol Tartrate) Oral Solution 10 mg/mL - NDC 30698-464-31 - 300 mL Bottle Label Physician Sample Not for Sale

LOPRESSOR® (Metoprolol Tartrate) Oral Solution 10 mg/mL - NDC 30698-464-31 - 300 mL Carton Label Physician Sample Not for Sale